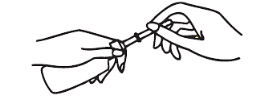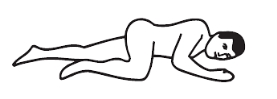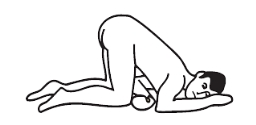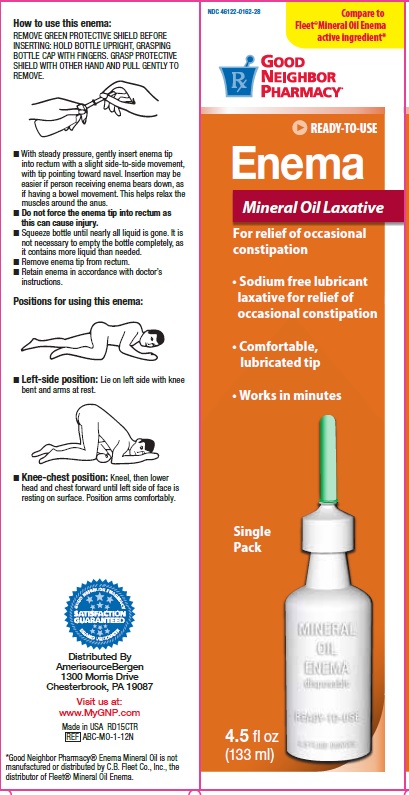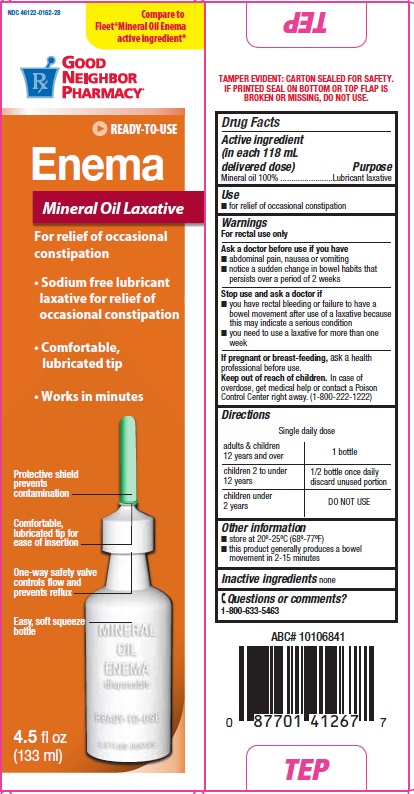 DRUG LABEL: Good Neighbor Mineral Oil
NDC: 46122-162 | Form: ENEMA
Manufacturer: AMERISOURCEBERGEN DRUG CORPORATION
Category: otc | Type: HUMAN OTC DRUG LABEL
Date: 20150714

ACTIVE INGREDIENTS: MINERAL OIL 118 mL/118 mL

Drug Facts

Active ingredient

(in each 118 mL delivered dose)

Mineral oil 100%

Purpose

Lubricant laxative

Uses

- for relief of occasional constipation

Warnings

For rectal use only

Ask a doctor before use if you have

- abdominal pain, nausea or vomiting
- notice a sudden change in bowel habits that persists over a period of 2 weeks

Stop use and ask a doctor if

- you have rectal bleeding or failure to have a bowel movement after use of a laxative because this may indicate a serious condition
- you need to use a laxative for more than one week

Keep out of reach of children.

In case of overdose, get medical help or contact a Poison Control Center right away. (1-800-222-1222)

Directions

Single daily dose

adults & children; 12 years and over | 1 bottle once daily
children 2 to under; 12 years | 1/2 bottle once daily; Discard Unused Portion
children under; 2 years | do not use

How to use this enema:

REMOVE GREEN PROTECTIVE SHIELD BEFORE INSERTING; HOLD BOTTLE UPRIGHT, GRASPING BOTTLE CAP WITH FINGERS. GRASP PROTECTIVE SHIELD WITH OTHER HAND AND PULL GENTLY TO REMOVE.

Positioning:

Left-side position: Lie on left side with knee bent and arms at rest.

Knee-chest position:

Kneel, then lower head and chest forward until left side of face is resting on surface. Position arms comfortably.

Administering enema:

- With steady pressure, gently insert enema tip into rectum with a slight side-to-side movement, with tip pointing toward navel. Insertion may be easier if person receiving enema bears down, as if having a bowel movement. This helps relax the muscles around the anus.
- Do not force the enema tip into rectum as this can cause injury.
- Squeeze bottle until nearly all liquid is gone. It is not necessary to empty the bottle completely, as it contains more liquid than needed.
- Remove enema tip from rectum.
- Retain enema in accordance with doctor's instructions.

Other Information

- store at room temperature 20-25 deg C (68-77 deg F)
- this product generally produces bowel movement in 2-15 minutes

Inactive ingredient

none

Questions or comments?

1-800-633-5463

Principal Display Panel

NDC 46122-0162-28

Compare to Fleet® Mineral Oil Enema active ingredient

Good Neighbor Pharmacy

Ready-To-Use

Enema

Mineral Oil Laxative

For relief of occasional constipation

Sodium Free Lubricant

Laxative For Relief

of Occasional Constipation

Comfortable, Lubricated Tip

Works In Minutes

Single pack

4.5 FL OZ (133ml)